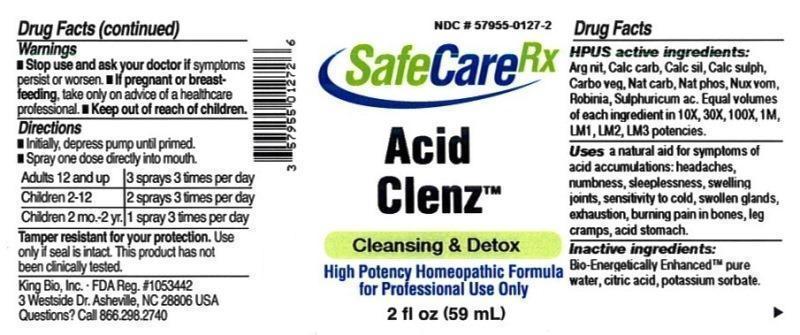 DRUG LABEL: Acid Clenz
NDC: 57955-0127 | Form: LIQUID
Manufacturer: King Bio Inc.
Category: homeopathic | Type: HUMAN OTC DRUG LABEL
Date: 20160518

ACTIVE INGREDIENTS: SILVER NITRATE 10 [hp_X]/59 mL; OYSTER SHELL CALCIUM CARBONATE, CRUDE 10 [hp_X]/59 mL; CALCIUM SILICATE 10 [hp_X]/59 mL; CALCIUM SULFATE ANHYDROUS 10 [hp_X]/59 mL; ACTIVATED CHARCOAL 10 [hp_X]/59 mL; SODIUM CARBONATE 10 [hp_X]/59 mL; SODIUM PHOSPHATE, DIBASIC, HEPTAHYDRATE 10 [hp_X]/59 mL; STRYCHNOS NUX-VOMICA SEED 10 [hp_X]/59 mL; ROBINIA PSEUDOACACIA BARK 10 [hp_X]/59 mL; SULFURIC ACID 10 [hp_X]/59 mL
INACTIVE INGREDIENTS: WATER; ANHYDROUS CITRIC ACID; POTASSIUM SORBATE

Acid Clenz™

ACTIVE INGREDIENT

Drug Facts__________________________________________________________________________________________________________

HPUS active ingredients: Argentum nitricum, Calcarea carbonica, Calcarea silicate, Calcarea sulphurica, Carbo vegetabilis, Natrum carbonicum, Natrum phosphoricum, Nux vomica, Robinia pseudoacacia, Sulphuricum acidum. Equal volumes of each ingredient in 10X, 30X, 100X, 1M, LM1, LM2, LM3 potencies.

INDICATIONS AND USAGE

Uses a natural aid for symptoms of acid accumulations: headaches, numbness, sleeplessness, swelling joints, sensitivity to cold, swollen glands, exhaustion, burning pain in bones, leg cramps, acid stomach.

Inactive Ingredients:

Bio-Energetically Enhanced™ pure water, citric acid and potassium sorbate.

Warnings

- Stop use and ask your doctor if symptoms persist or worsen.
- If pregnant or breast-feeding, take only on advice of a healthcare professional.

- Keep out of reach of children.

Directions

- Initially, depress pump until primed.
- Spray one dose directly into mouth.
- Adults 12 and up: 3 sprays 3 times per day.
- Children 2-12 yr: 2 sprays 3 times per day.
- Children 2 mo-2 yr: 1 spray 3 times per day.

OTHER SAFETY INFORMATION

Tamper resistant for your protection. Use only if safety seal is intact. This product has not been clinically tested.

PURPOSE

Uses a natural aid for symptoms of acid accumulations:

- headaches
- numbness
- sleeplessness
- swelling joints
- sensitivity to cold
- swollen glands
- exhaustion
- burning pain in bones
- leg cramps
- acid stomach